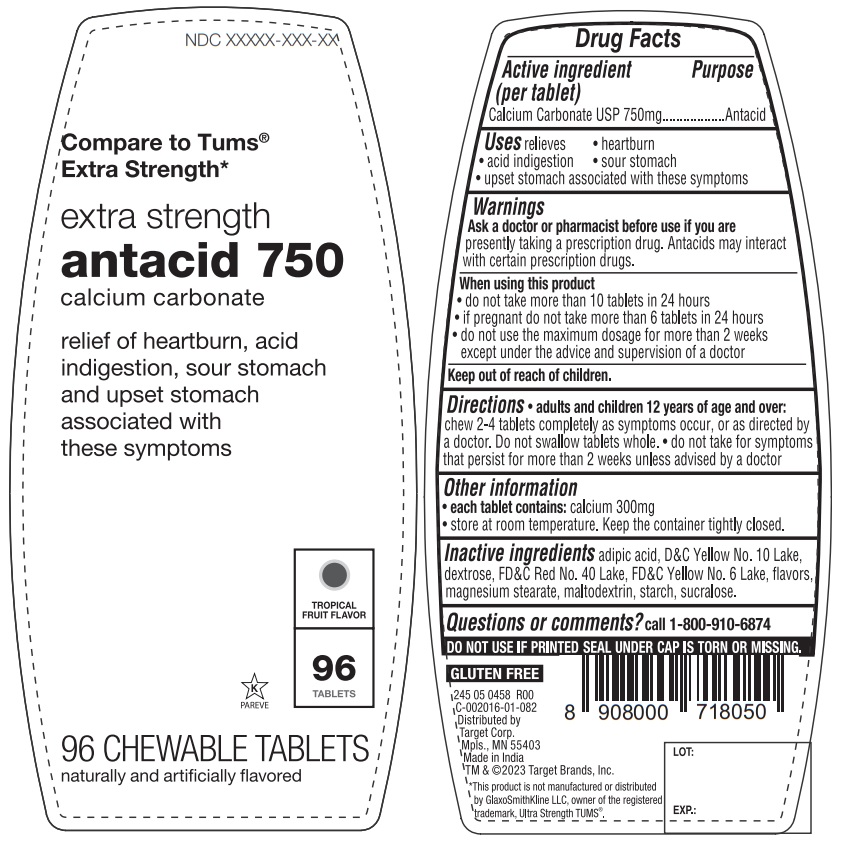 DRUG LABEL: up and up extra strength antacid 750
NDC: 82442-102 | Form: TABLET, CHEWABLE
Manufacturer: Target Corporation
Category: otc | Type: HUMAN OTC DRUG LABEL
Date: 20230407

ACTIVE INGREDIENTS: CALCIUM CARBONATE 750 mg/1 1
INACTIVE INGREDIENTS: ADIPIC ACID; D&C YELLOW NO. 10 ALUMINUM LAKE; DEXTROSE, UNSPECIFIED FORM; FD&C RED NO. 40; FD&C YELLOW NO. 6; MAGNESIUM STEARATE; MALTODEXTRIN; STARCH, CORN; SUCRALOSE

extra strength antacid 750

Active ingredient (per tablet)

Calcium Carbonate USP 750mg

Purpose

Antacid

Uses

relieves • heartburn • acid indigestion • sour stomach • upset stomach associated with these symptoms

Warnings

Ask a doctor or pharmacist before use if you are presently taking a prescription drug. Antacids may interact with certain prescription drugs.

When using this product

• do not take more than 10 tablets in 24 hours
• if pregnant do not take more than 6 tablets in 24 hours
• do not use the maximum dosage for more than 2 weeks except under the advice and supervision of a doctor

Keep out of reach of children.

Directions

• adults and children 12 years of age and over: chew 2-4 tablets completely as symptoms occur, or as directed by a doctor. Do not swallow tablets whole. • do not take for symptoms that persist for more than 2 weeks unless advised by a doctor

Other information

• each tablet contains: calcium 300mg
• store at room temperature. Keep the container tightly closed.

Inactive ingredients

adipic acid, D&C Yellow No. 10 Lake, dextrose, FD&C Red No. 40 Lake, FD&C Yellow No. 6 Lake, flavors, magnesium stearate, maltodextrin, starch, sucralose.

Questions or comments?

call 1-800-910-6874

Compare to Tums® Extra Strength*

TROPICAL FRUIT FLAVOR

naturally and artificially flavored

DO NOT USE IF PRINTED SEAL UNDER CAP IS TORN OR MISSING.

GLUTEN FREE

Distributed by
Target Corp.
Mpls., MN 55403
Made in India

TM & ©2023 Target Brands, Inc.

*This product is not manufactured or distributed by GlaxoSmithKline LLC, owner of the registered trademark, Ultra Strength TUMS®.